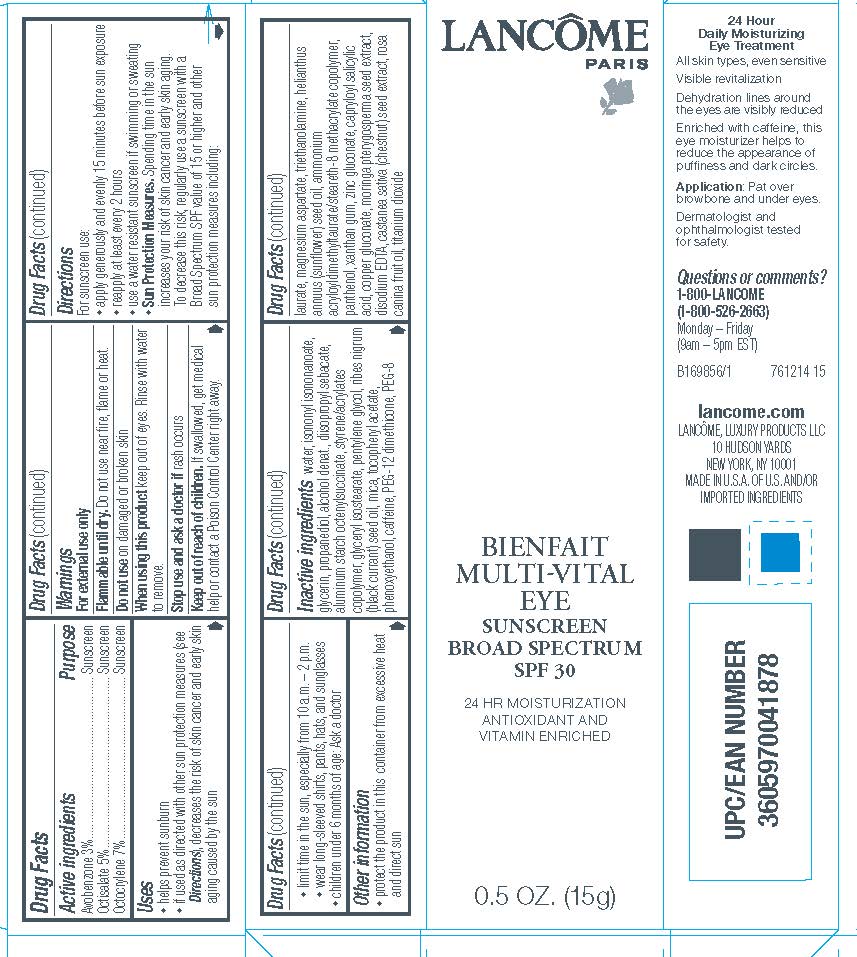 DRUG LABEL: Lancome Paris Bienfait MultiVital Eye Broad Spectrum SPF 30 Sunscreen
NDC: 49967-878 | Form: CREAM
Manufacturer: L'Oreal USA Products Inc
Category: otc | Type: HUMAN OTC DRUG LABEL
Date: 20231230

ACTIVE INGREDIENTS: AVOBENZONE 30 mg/1 g; OCTISALATE 50 mg/1 g; OCTOCRYLENE 70 mg/1 g
INACTIVE INGREDIENTS: WATER; ISONONYL ISONONANOATE; GLYCERIN; PROPANEDIOL; ALCOHOL; DIISOPROPYL SEBACATE; ALUMINUM STARCH OCTENYLSUCCINATE; STYRENE/ACRYLAMIDE COPOLYMER (500000 MW); GLYCERYL ISOSTEARATE; PENTYLENE GLYCOL; RIBES NIGRUM SEED OIL; MICA; .ALPHA.-TOCOPHEROL ACETATE; PHENOXYETHANOL; CAFFEINE; PEG-12 DIMETHICONE; PEG-8 LAURATE; MAGNESIUM ASPARTATE; TROLAMINE; SUNFLOWER OIL; PANTHENOL; XANTHAN GUM; ZINC GLUCONATE; CAPRYLOYL SALICYLIC ACID; COPPER GLUCONATE; MORINGA OLEIFERA SEED; EDETATE DISODIUM; SPANISH CHESTNUT; ROSA CANINA FRUIT OIL; TITANIUM DIOXIDE

Drug Facts

Active ingredients

Avobenzone 3%

Octisalate 5%

Octocrylene 7%

Purpose

Sunscreen

Uses

- helps prevent sunburn
- if used as directed with other sun protection measures (see Directions), decreases the risk of skin cancer and early skin aging caused by the sun

Warnings

For external use only

Flammable until dry.

Do not use near fire, flame, or heat.

Do not use

on damaged or broken skin

When using this product

keep out of eyes. Rinse with water to remove.

Stop use and ask a doctor if

rash occurs

Keep out of reach of children.

If swallowed, get medical help or contact a Poison Control Center right away.

Directions

For sunscreen use:

● apply generously and evenly 15 minutes before sun exposure

● reapply at least every 2 hours

● use a water resistant sunscreen if swimming or sweating

● Sun Protection Measures. Spending time in the sun increases your risk of skin cancer and early skin aging. To decrease this risk, regularly use a sunscreen with a Broad Spectrum SPF value of 15 or higher and other sun protection measures including:

● limit time in the sun, especially from 10 a.m. – 2 p.m.

● wear long-sleeved shirts, pants, hats, and sunglasses

● children under 6 months of age: Ask a doctor

Other information

protect the product in this container from excessive heat and direct sun

Inactive ingredients

water, isononyl isononanoate, glycerin, propanediol, alcohol denat., diisopropyl sebacate, aluminum starch octenylsuccinate, styrene/acrylates
copolymer, glyceryl isostearate, pentylene glycol, ribes nigrum (black currant) seed oil, mica, tocopheryl acetate, phenoxyethanol, caffeine, PEG-12 dimethicone, PEG-8 laurate, magnesium aspartate, triethanolamine, helianthus annuus (sunflower) seed oil, ammonium acryloyldimethyltaurate/steareth-8 methacrylate copolymer, panthenol, xanthan gum, zinc gluconate, capryloyl salicylic acid, copper gluconate, moringa pterygosperma seed extract, disodium EDTA, castanea sativa (chestnut) seed extract, rosa canina fruit oil, titanium dioxide